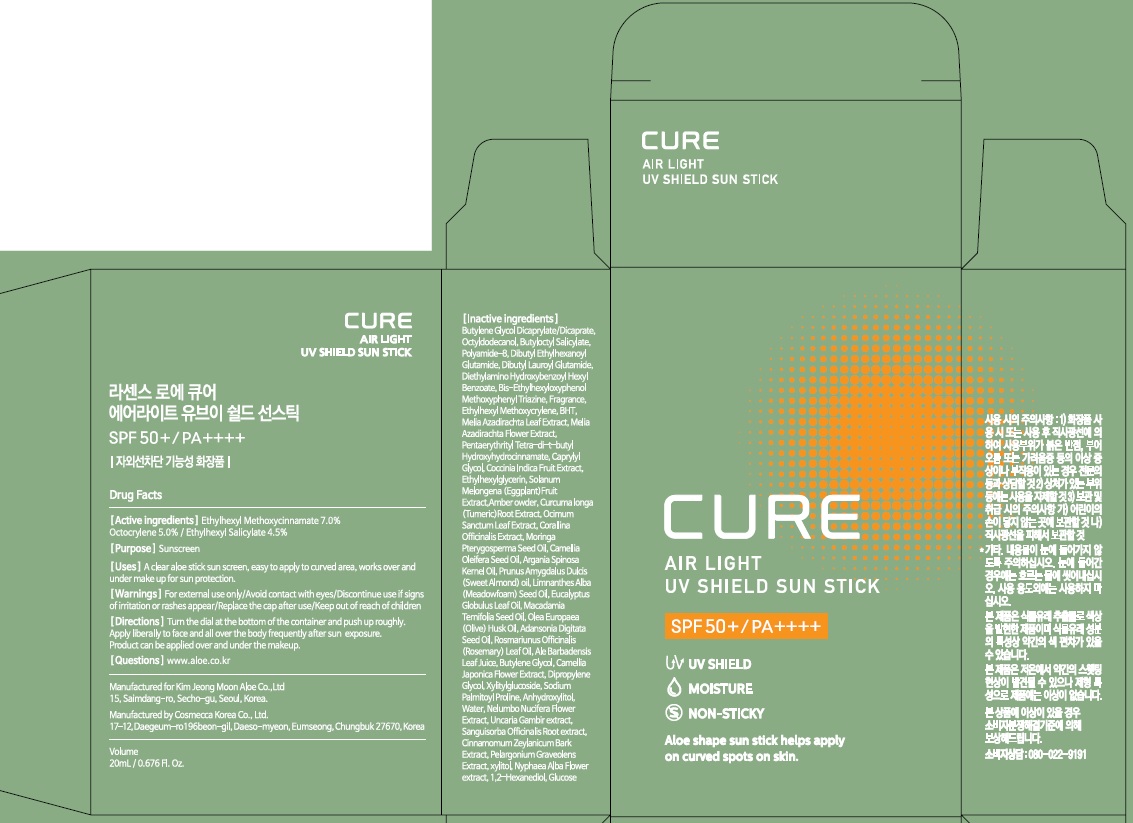 DRUG LABEL: Ra Sence Loe Cure Air light UV shield Sun
NDC: 50410-120 | Form: STICK
Manufacturer: Kimjeongmoon Aloe Co., Ltd.
Category: otc | Type: HUMAN OTC DRUG LABEL
Date: 20181122

ACTIVE INGREDIENTS: Octinoxate 1.4 g/20 mL; Octocrylene 1.0 g/20 mL; Octisalate 0.9 g/20 mL
INACTIVE INGREDIENTS: Butylene Glycol; Octyldodecanol

ACTIVE INGREDIENT

Active ingredients: Ethylhexyl Methoxycinnamate 7.0%, Octocrylene 5.0%, Ethylhexyl Salicylate 4.5%

INACTIVE INGREDIENT

Inactive ingredients:

Butylene Glycol Dicaprylate/Dicaprate, Octyldodecanol, Butyloctyl Salicylate, Polyamide-8, Dibutyl Ethylhexanoyl Glutamide, Dibutyl Lauroyl Glutamide, Diethylamino Hydroxybenzoyl Hexyl Benzoate, Bis-Ethylhexyloxyphenol Methoxyphenyl Triazine, Fragrance, Ethylhexyl Methoxycrylene, BHT, Melia Azadirachta Leaf Extract, Melia Azadirachta Flower Extract, Pentaerythrityl Tetra-di-t-butyl Hydroxyhydrocinnamate, Caprylyl Glycol, Coccinia Indica Fruit Extract, Ethylhexylglycerin, Solanum Melongena (Eggplant)Fruit Extract,Amber owder, Curcuma longa (Tumeric)Root Extract, Ocimum Sanctum Leaf Extract, Corallina Officinalis Extract, Moringa Pterygosperma Seed Oil, Camellia Oleifera Seed Oil, Argania Spinosa Kernel Oil, Prunus Amygdalus Dulcis (Sweet Almond) oil, Limnanthes Alba (Meadowfoam) Seed Oil, Eucalyptus Globulus Leaf Oil, Macadamia Ternifolia Seed Oil, Olea Europaea (Olive) Husk Oil, Adansonia Digitata Seed Oil, Rosmariunus Officinalis (Rosemary) Leaf Oil, Ale Barbadensis Leaf Juice, Butylene Glycol, Camellia Japonica Flower Extract, Dipropylene Glycol, Xylitylglucoside, Sodium Palmitoyl Proline, Anhydroxylitol, Water, Nelumbo Nucifera Flower Extract, Uncaria Gambir extract, Sanguisorba Officinalis Root extract, Cinnamomum Zeylanicum Bark Extract, Pelargonium Graveolens Extract, xylitol, Nyphaea Alba Flower extract, 1,2-Hexanediol, Glucose

PURPOSE

Purpose: Sunscreen

WARNINGS

For external use only

Avoid contact with eyes.

Discontinue use if signs of irritation or rashes appear.

Replace the cap after use.

Keep out of reach of children

DESCRIPTION

Uses:

A clear aloe stick sun screen, easy to apply to curved area, works over and under make up for sun protection.

Directions:

-Turn the dial at the bottom of the container and push up roughly.

-Apply liberally to face and all over the body frequently after sun exposure.

-Product can be applied over and under the makeup.